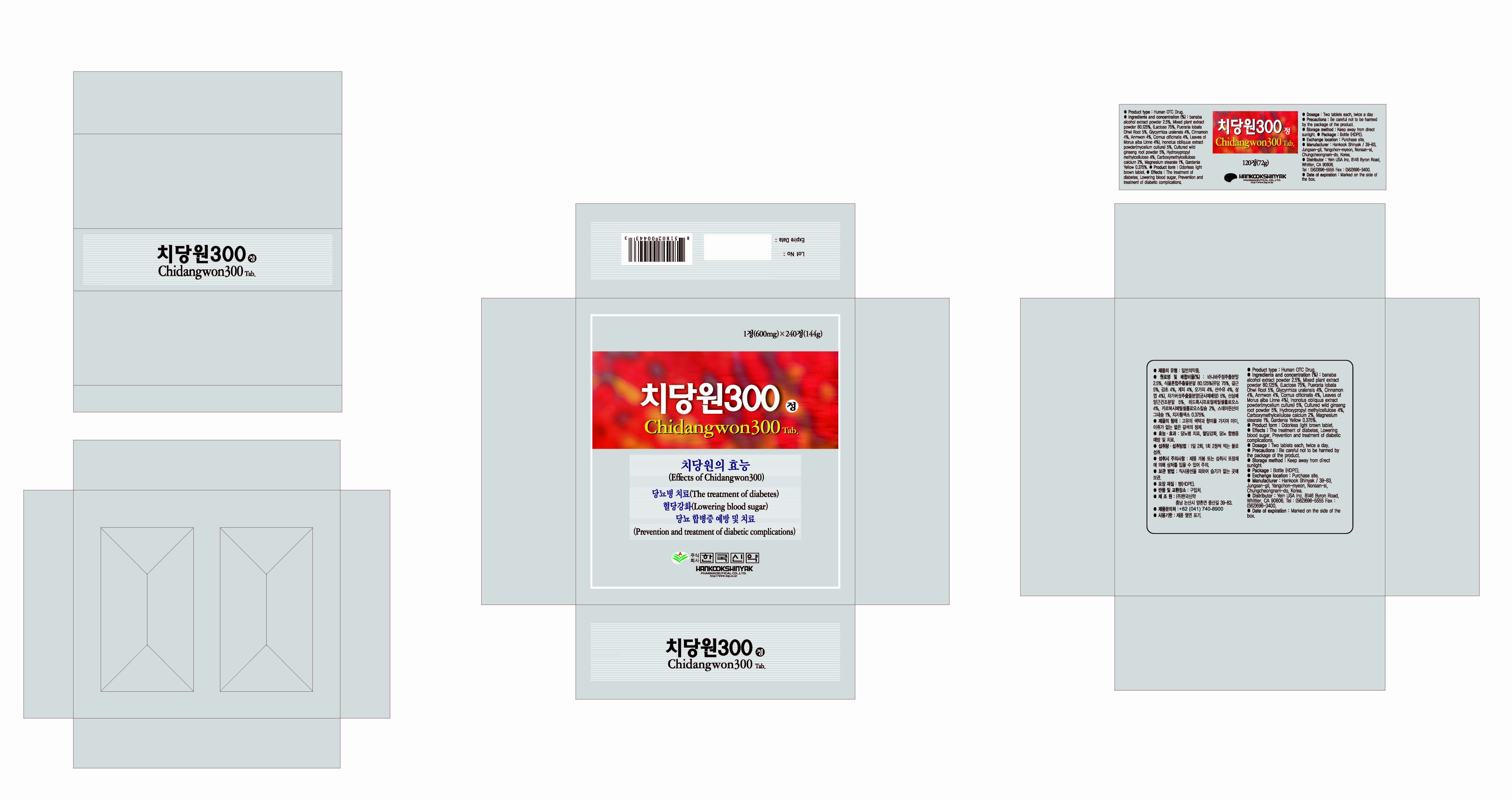 DRUG LABEL: Chidangwon 300
                
NDC: 53144-4001 | Form: TABLET
Manufacturer: Yein Trading & Global Co., Ltd
Category: otc | Type: HUMAN OTC DRUG LABEL
Date: 20130105

ACTIVE INGREDIENTS: LAGERSTROEMIA INDICA WHOLE 0.018 1/1 1
INACTIVE INGREDIENTS: LACTOSE; PUERARIA MONTANA VAR. LOBATA ROOT; GLYCYRRHIZA URALENSIS; CINNAMON; CORNUS OFFICINALIS FRUIT; MORUS ALBA WHOLE; HYPROMELLOSES; CARBOXYMETHYLCELLULOSE CALCIUM; MAGNESIUM STEARATE

Drug Facts

ACTIVE INGREDIENT

banaba alcohol extract powder

INACTIVE INGREDIENT

Mixed plant extract powder 80.125% (Lactose 75%, Pueraria lobata Ohwi Root 5%, Glycyrrhiza uralensis 4%, Cinnamon 4%, Anmwon 4%, Cornus officinalis 4%, Leaves of Morus alba Linne 4%), Chaga mushroom extract powder (mycelium culture) 5%, Cultured Wild ginseng root powder 5%, Hydroxypropylmethyl-cellulose 4%, Carboxymethylcellulose calcium 2%, Magnesium stearate 1%, Gardenia Yellow 0.375%

PURPOSE

- treatment of diabetes
- lowering blood sugar
- prevention and treatment of diabetic complications

keep out of reach of the children